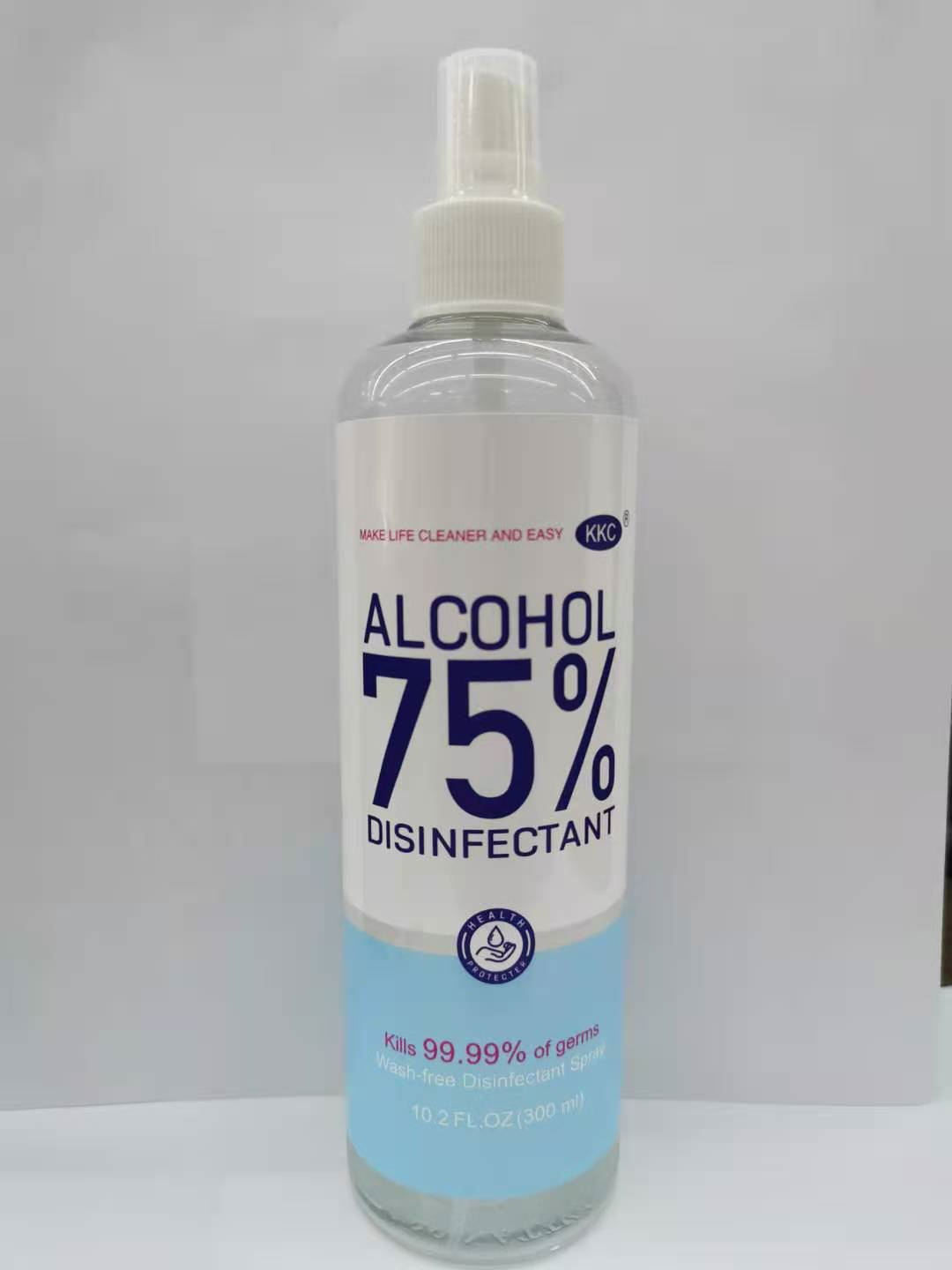 DRUG LABEL: Hand sanitizer
NDC: 55469-008 | Form: GEL
Manufacturer: DONGYANG LIULU COSMETICS CO.LTD
Category: otc | Type: HUMAN OTC DRUG LABEL
Date: 20201126

ACTIVE INGREDIENTS: ALCOHOL 225 mL/300 mL
INACTIVE INGREDIENTS: WATER

Uses

to decrease bacteria on the skin that could cause disease.

recommended for repeated use.

WARNINGS

For external use only. Flammable.Keep away from fire or flame

WHEN USING

keep out of eyes.

ln case of contact with eyes.

flush thoroughly with water.

avoid contact with broken skin .

do not inhale or ingest.

STOP USE

irritation or redness develops .

condition persists for more than 72 hours.

KEEP OUT OF REACH OF CHILDREN

If swallowed. get medical help or contact a Poison Control Center right away.

INDICATIONS AND USAGE

Place enough product on hands to cover all surfaces.Rub hands together until dry.Supervise children under 6 years of agewhen using this product to avoid swallowing.

other information

Do not store above 105°F

May discolor some fabrics

Harmful to wood finishes and plastics.

INACTIVE INGREDIENT

purified water

ACTIVE INGREDIENT

ALCOHOL 75%

PURPOSE

Disinfection
Sterilization